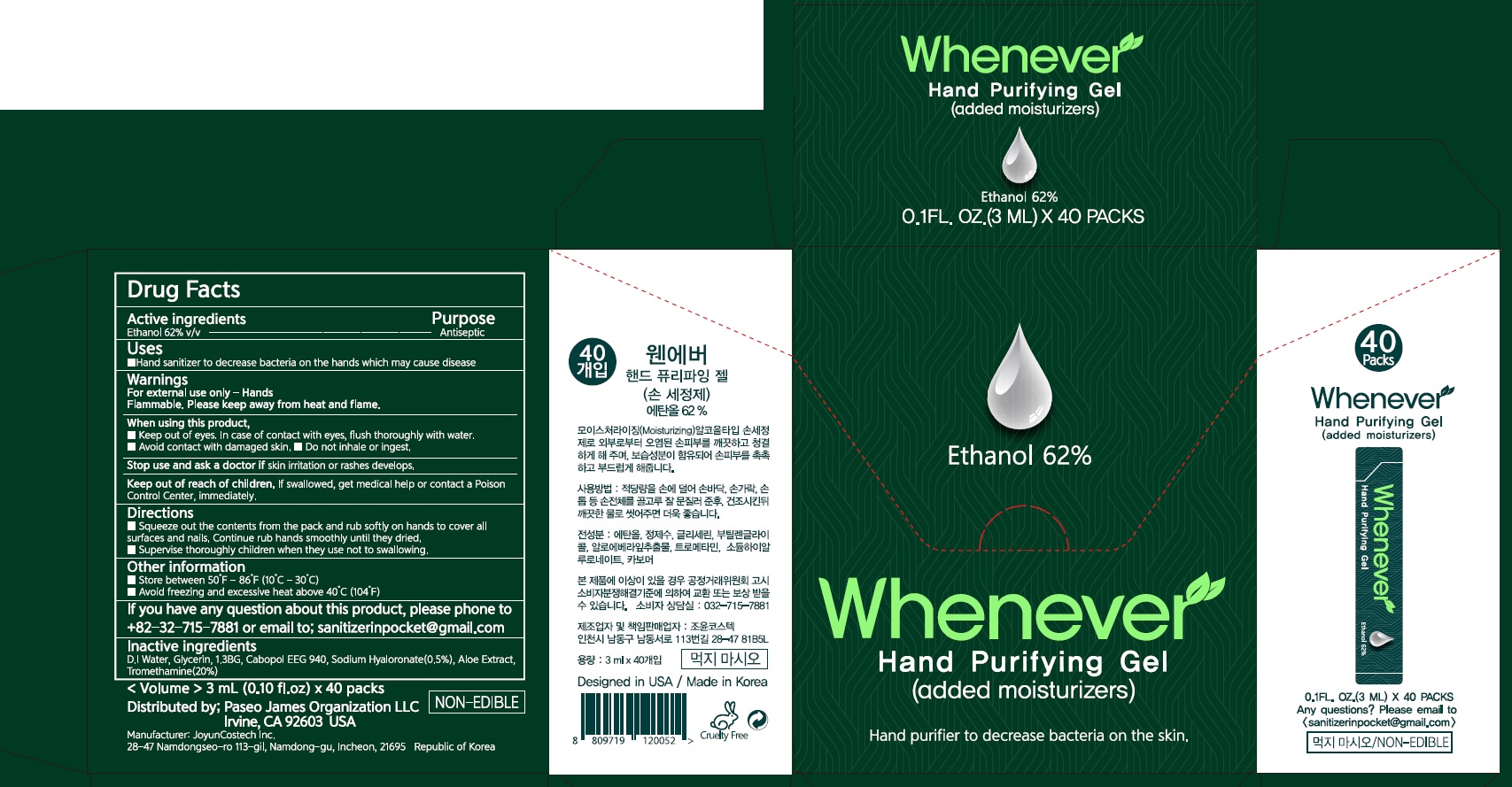 DRUG LABEL: Whenever Hand Purifying
NDC: 90038-010 | Form: GEL
Manufacturer: JoyunCostech
Category: otc | Type: HUMAN OTC DRUG LABEL
Date: 20201207

ACTIVE INGREDIENTS: ALCOHOL 62 mL/100 mL
INACTIVE INGREDIENTS: Water; Glycerin; HYALURONATE SODIUM; ALOE; TROMETHAMINE

ACTIVE INGREDIENT

Ethanol 62 % v/v

INACTIVE INGREDIENTS

D.I Water, Glycerin, 1.3BG, Cabopol EEG 940, Sodium Hyaluronate(0.5%), Aloe Extract, Tromethamine(20%)

PURPOSE

Antiseptic

WARNINGS

For external use only-hands
Flammable. Please keep away from heat and flame.

When using this product ■ Keep out of eyes. In case of contact with eyes, flush thoroughly with water. ■ Avoid contact with damaged skin. ■ Do not inhale or ingest.

Stop use and ask a doctor if skin irritation or rash develops.

Keep out of reach of children. If swallowed, get medical help or contact a Poison Control Center immediately.

KEEP OUT OF REACH OF CHILDREN

If swallowed, get medical help or contact a Poison Control Center immediately.

Uses

■ Hand sanitizer to decrease bacteria on hands which may cause disease

Directions

■ Squeeze out the contents from the pack and rub softly on hands to cover all surfaces and nails. Continue rub hands smoothly until they dried.
■ Supervise thoroughly children when they use not to swallowing.

Other information

■ Store between 50F~86F (10C~30C)
■ Avoid freezing and excessive heat above 40C (104F)

QUESTIONS

If you have any question about this product, please phone to +82-32-715-7881 or email to; sanitizerinpocket@gmail.com